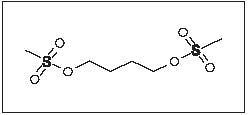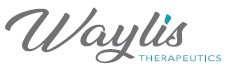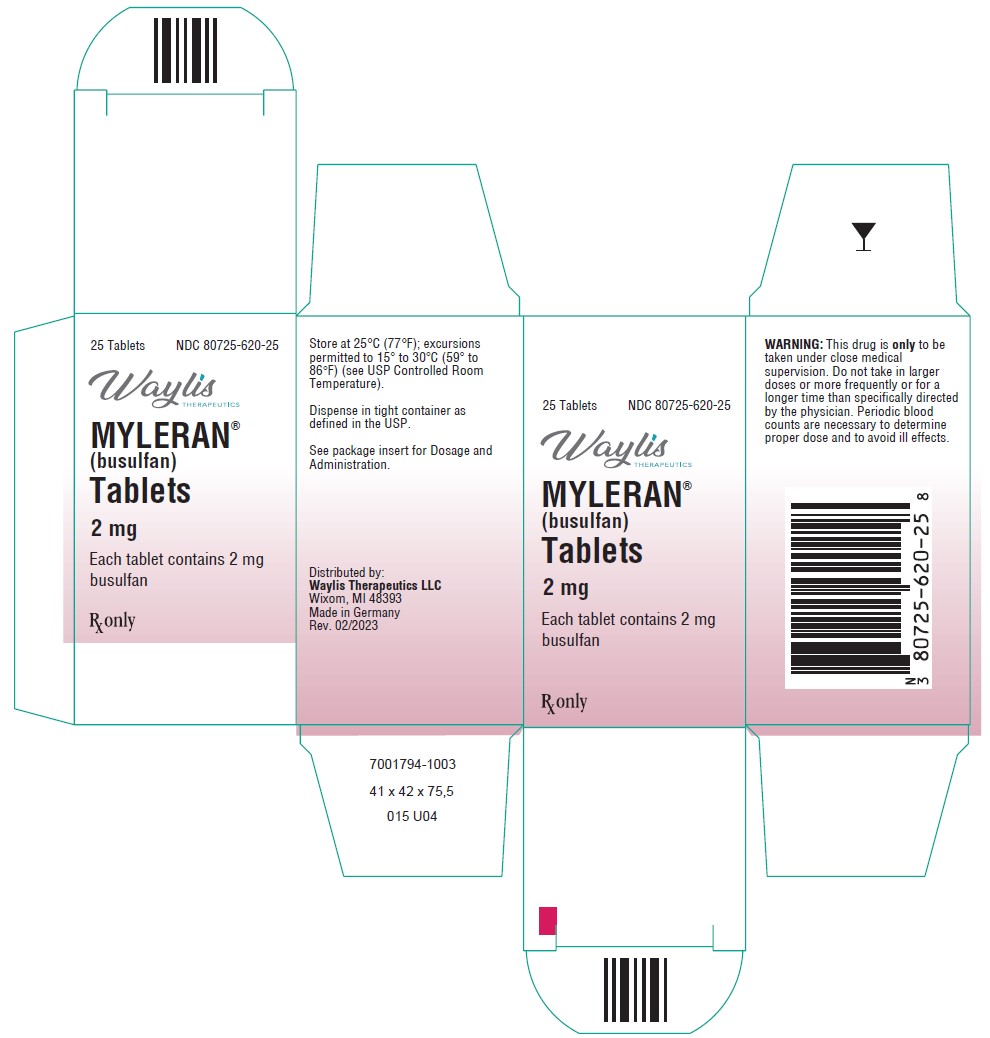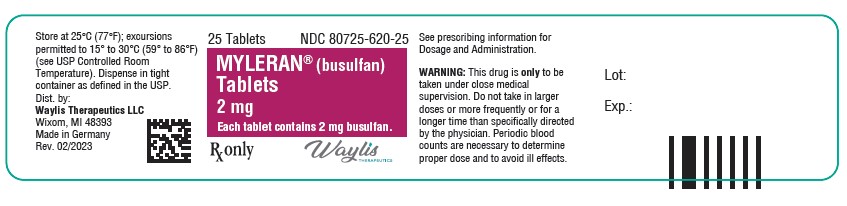 DRUG LABEL: MYLERAN
NDC: 80725-620 | Form: TABLET, FILM COATED
Manufacturer: Waylis Therapeutics LLC
Category: prescription | Type: HUMAN PRESCRIPTION DRUG LABEL
Date: 20250108

ACTIVE INGREDIENTS: BUSULFAN 2 mg/1 1
INACTIVE INGREDIENTS: HYPROMELLOSES; ANHYDROUS LACTOSE; MAGNESIUM STEARATE; STARCH, CORN; TRIACETIN; TITANIUM DIOXIDE

MYLERAN®
(busulfan) Tablets

WARNING

MYLERAN is a potent drug. It should not be used unless a diagnosis of chronic myelogenous leukemia has been adequately established and the responsible physician is knowledgeable in assessing response to chemotherapy.

MYLERAN can induce severe bone marrow hypoplasia. Reduce or discontinue the dosage immediately at the first sign of any unusual depression of bone marrow function as reflected by an abnormal decrease in any of the formed elements of the blood. A bone marrow examination should be performed if the bone marrow status is uncertain.

SEE WARNINGS FOR INFORMATION REGARDING BUSULFAN-INDUCED LEUKEMOGENESIS IN HUMANS.

DESCRIPTION

MYLERAN (busulfan) is a bifunctional alkylating agent. Busulfan is known chemically as 1,4-butanediol dimethanesulfonate and has the following structural formula:

CH3SO2O(CH2)4OSO2CH3

Busulfan is not a structural analog of the nitrogen mustards. MYLERAN is available in tablet form for oral administration. Each film-coated tablet contains 2 mg busulfan and the inactive ingredients hypromellose, lactose (anhydrous), magnesium stearate, pregelatinized starch, triacetin, and titanium dioxide.

The activity of busulfan in chronic myelogenous leukemia was first reported by D.A.G. Galton in 1953.

CLINICAL PHARMACOLOGY

Busulfan is a small, highly lipophilic molecule that easily crosses the blood brain barrier. Following absorption, 32% and 47% of busulfan are bound to plasma proteins and red blood cells, respectively.

Busulfan absorption from the gastrointestinal tract is essentially complete. This has been demonstrated in radioactive studies after both intravenous and oral administration of ^35S-busulfan, ^14C-busulfan, and ^3H-busulfan. Following intravenous administration of a single therapeutic dose of ^35S-busulfan, there was rapid disappearance of radioactivity from the blood and 90% to 95% of the ^35S-label disappeared within 3 to 5 minutes after injection. After either oral or intravenous administration of ^35S-busulfan, 45% to 60% of the radioactivity was recovered in the urine in the 48 hours after administration; the majority of the total urinary excretion occurring in the first 24 hours. Over 95% of the urinary ^35S-label occurs as ^35S-methanesulfonic acid. Oral and intravenous administration of 1,4-^14C-busulfan showed the same rapid initial disappearance of plasma radioactivity as observed following the administration of ^35S-labeled drug. Cumulative radioactivity in the urine after 48 hours was 25% to 30% of the administered dose (contrasting with 45% to 60% for ^35S-busulfan), and suggests a slower excretion of the alkylating portion of the molecule and its metabolites than for the sulfonoxymethyl moieties.
Regardless of the route of administration, 1,4-^14C-busulfan yielded a complex mixture of at least 12 radiolabeled metabolites in urine; the main metabolite being 3-hydroxytetrahydrothiophene-1,1-dioxide.

Pharmacokinetic studies employing ^3H-busulfan labeled on the tetramethylene chain confirmed a rapid initial clearance of the radioactivity from plasma, irrespective of whether the drug was given orally or intravenously.

A study compared a 2-mg single IV bolus injection to a single oral dose of a 2-mg tablet of nonradioactive busulfan in 8 adult patients 13 to 60 years of age. The study demonstrated that the mean ± SD absolute bioavailability was 80% ± 20% in adults. However, the absolute bioavailability for 8 children 1.5 to 6 years of age was 68% ± 31%.

In another study of 2, 4, and 6 mg of busulfan, given as a single oral dose on consecutive days (starting with the lowest dose) in 5 adult patients, the mean dose-normalized (to 2 mg dose) area under the plasma concentration-time curve (AUC) was about 130 ng•hr/mL, while the mean intra- and inter-patient variability was about 16% and 21%, respectively. Busulfan was eliminated with a plasma terminal elimination half-life (t1/2) of about 2.6 hours, and demonstrated linear kinetics within the range of 2 to 6 mg for both the maximum plasma concentration (Cmax) and AUC. The mean Cmax for the 2-, 4-, and 6-mg doses (after dose normalization to 2 mg) was about 30 ng/mL. A recent study of 4 to 8 mg as single oral doses in 12 patients showed that the mean ± SD Cmax (after dose normalization to 4 mg) was 68.2 ± 24.4 ng/mL, occurring at about 0.9 hours and the mean ± SD AUC (after dose normalization to 4 mg) was 269 ± 62 ng•hr/mL. These results are consistent with previous results. In addition, the mean ± SD elimination half-life was 2.69 ± 0.49 hours.

The elimination of busulfan appears to be independent of renal function. This probably reflects the extensive metabolism of the drug in the liver, since less than 2% of the administered dose is excreted in the urine unchanged within 24 hours. The drug is metabolized by enzymatic activity to at least 12 metabolites, among which tetrahydrothiophene, tetrahydrothiophene 12-oxide, sulfolane, and 3-hydroxysulfolane were identified. These metabolites do not have cytotoxic activity.

There is no experience with the use of dialysis in an attempt to modify the clinical toxicity of busulfan. One technical difficulty would derive from the extremely poor water solubility of busulfan.
Additionally, all studies of the metabolism of busulfan employing radiolabeled materials indicate rapid chemical reactivity of the parent compound with prolonged retention of some of the metabolites (particularly the metabolites arising from the “alkylating” portion of the molecule). The effectiveness of dialysis at removing significant quantities of unreacted drug would be expected to be minimal in such a situation. Currently, there are no available data on the effect of food on busulfan bioavailability.

Pharmacokinetics in Hemodialysis Patients

The impact of hemodialysis on the clearance of busulfan was determined in a patient with chronic renal failure undergoing autologous stem cell transplantation. The apparent oral clearance of busulfan during a 4-hour hemodialysis session was increased by 65%, but the 24-hour oral clearance of busulfan was increased by only 11%.

The incidence of veno-occlusive disease was higher (33.3% versus 3.0%) in patients with busulfan AUC0-6hr >1,500 μM.min (Css >900 mcg/L) compared to patients with busulfan AUC0-6hr <1,500 μM.min (Css <900 mcg/L) (see WARNINGS).

Drug Interactions

Itraconazole reduced busulfan clearance by up to 25% in patients receiving itraconazole compared to patients who did not receive itraconazole. Higher busulfan exposure due to concomitant itraconazole could lead to toxic plasma levels in some patients. Fluconazole had no effect on the clearance of busulfan. Patients treated with concomitant cyclophosphamide and busulfan with phenytoin pretreatment have increased cyclophosphamide and busulfan clearance, which may lead to decreased concentrations of both cyclophosphamide and busulfan. However, busulfan clearance may be reduced in the presence of cyclophosphamide alone, presumably due to competition for glutathione.

Diazepam had no effect on the clearance of busulfan.

No information is available regarding the penetration of busulfan into brain or cerebrospinal fluid.

Biochemical Pharmacology

In aqueous media, busulfan undergoes a wide range of nucleophilic substitution reactions. While this chemical reactivity is relatively non-specific, alkylation of the DNA is felt to be an important biological mechanism for its cytotoxic effect. Coliphage T7 exposed to busulfan was found to have the DNA crosslinked by intrastrand crosslinkages, but no interstrand linkages were found.

The metabolic fate of busulfan has been studied in rats and humans using ^14C- and ^35S-labeled materials. In humans, as in the rat, almost all of the radioactivity in ^35S-labeled busulfan is excreted in the urine in the form of ^35S-methanesulfonic acid. Roberts and Warwick demonstrated that the formation of methanesulfonic acid in vivo in the rat is not due to a simple hydrolysis of busulfan to 1,4-butanediol, since only about 4% of 2,3-^14C-busulfan was excreted as carbon dioxide, whereas 2,3-^14C-1,4-butanediol was converted almost exclusively to carbon dioxide. The predominant reaction of busulfan in the rat is the alkylation of sulfhydryl groups (particularly cysteine and cysteine-containing compounds) to produce a cyclic sulfonium compound which is the precursor of the major urinary metabolite of the 4-carbon portion of the molecule, 3-hydroxytetrahydrothiophene-1,1-dioxide. This has been termed a “sulfur-stripping” action of busulfan and it may modify the function of certain sulfur-containing amino acids, polypeptides, and proteins; whether this action makes an important contribution to the cytotoxicity of busulfan is unknown.

The biochemical basis for acquired resistance to busulfan is largely a matter of speculation. Although altered transport of busulfan into the cell is one possibility, increased intracellular inactivation of the drug before it reaches the DNA is also possible. Experiments with other alkylating agents have shown that resistance to this class of compounds may reflect an acquired ability of the resistant cell to repair alkylation damage more effectively.

Clinical Studies

Although not curative, busulfan reduces the total granulocyte mass, relieves symptoms of the disease, and improves the clinical state of the patient. Approximately 90% of adults with previously untreated chronic myelogenous leukemia will obtain hematologic remission with regression or stabilization of organomegaly following the use of busulfan. It has been shown to be superior to splenic irradiation with respect to survival times and maintenance of hemoglobin levels, and to be equivalent to irradiation at controlling splenomegaly.

It is not clear whether busulfan unequivocally prolongs the survival of responding patients beyond the 31 months experienced by an untreated group of historical controls. Median survival figures of 31 to 42 months have been reported for several groups of patients treated with busulfan, but concurrent control groups of comparable, untreated patients are not available. The median survival figures reported from different studies will be influenced by the percentage of “poor risk” patients initially entered into the particular study. Patients who are alive 2 years following the diagnosis of chronic myelogenous leukemia, and who have been treated during that period with busulfan, are estimated to have a mean annual mortality rate during the second to fifth year which is approximately two thirds that of patients who received either no treatment, conventional x-ray or ^32P-irradiation, or chemotherapy with minimally active drugs.

Busulfan is clearly less effective in patients with chronic myelogenous leukemia who lack the Philadelphia (Ph^1) chromosome. Also, the so-called “juvenile” type of chronic myelogenous leukemia, typically occurring in young children and associated with the absence of a Philadelphia chromosome, responds poorly to busulfan. The drug is of no benefit in patients whose chronic myelogenous leukemia has entered a “blastic” phase.

MYLERAN should not be used in patients whose chronic myelogenous leukemia has demonstrated prior resistance to this drug.

MYLERAN is of no value in chronic lymphocytic leukemia, acute leukemia, or in the “blastic crisis” of chronic myelogenous leukemia.

INDICATIONS AND USAGE

MYLERAN (busulfan) is indicated for the palliative treatment of chronic myelogenous (myeloid, myelocytic, granulocytic) leukemia.

CONTRAINDICATIONS

MYLERAN is contraindicated in patients in whom a definitive diagnosis of chronic myelogenous leukemia has not been firmly established.

MYLERAN is contraindicated in patients who have previously suffered a hypersensitivity reaction to busulfan or any other component of the preparation.

WARNINGS

The most frequent, serious side effect of treatment with busulfan is the induction of bone marrow failure (which may or may not be anatomically hypoplastic) resulting in severe pancytopenia. The pancytopenia caused by busulfan may be more prolonged than that induced with other alkylating agents. It is generally felt that the usual cause of busulfan-induced pancytopenia is the failure to stop administration of the drug soon enough; individual idiosyncrasy to the drug does not seem to be an important factor. MYLERAN should be used with extreme caution and exceptional vigilance in patients whose bone marrow reserve may have been compromised by prior irradiation or chemotherapy, or whose marrow function is recovering from previous cytotoxic therapy. Although recovery from busulfan-induced pancytopenia may take from 1 month to 2 years, this complication is potentially reversible, and the patient should be vigorously supported through any period of severe pancytopenia.

A rare, important complication of busulfan therapy is the development of bronchopulmonary dysplasia with pulmonary fibrosis. Symptoms have been reported to occur within 8 months to 10 years after initiation of therapy—the average duration of therapy being 4 years. The histologic findings associated with “busulfan lung” mimic those seen following pulmonary irradiation. Clinically, patients have reported the insidious onset of cough, dyspnea, and low-grade fever. In some cases, however, onset of symptoms may be acute. Pulmonary function studies have revealed diminished diffusion capacity and decreased pulmonary compliance. It is important to exclude more common conditions (such as opportunistic infections or leukemic infiltration of the lungs) with appropriate diagnostic techniques. If measures such as sputum cultures, virologic studies, and exfoliative cytology fail to establish an etiology for the pulmonary infiltrates, lung biopsy may be necessary to establish the diagnosis. Treatment of established busulfan-induced pulmonary fibrosis is unsatisfactory; in most cases the patients have died within 6 months after the diagnosis was established. There is no specific therapy for this complication. MYLERAN should be discontinued if this lung toxicity develops. The administration of corticosteroids has been suggested, but the results have not been impressive or uniformly successful.

Busulfan may cause cellular dysplasia in many organs in addition to the lung. Cytologic abnormalities characterized by giant, hyperchromatic nuclei have been reported in lymph nodes, pancreas, thyroid, adrenal glands, liver, and bone marrow. This cytologic dysplasia may be severe enough to cause difficulty in interpretation of exfoliative cytologic examinations from the lung, bladder, breast, and the uterine cervix.

In addition to the widespread epithelial dysplasia that has been observed during busulfan therapy, chromosome aberrations have been reported in cells from patients receiving busulfan. Busulfan is mutagenic in mice and, possibly, in humans. Malignant tumors and acute leukemias have been reported in patients who have received busulfan therapy, and this drug may be a human carcinogen. The World Health Organization has concluded that there is a causal relationship between busulfan exposure and the development of secondary malignancies. Four cases of acute leukemia occurred among 243 patients treated with busulfan as adjuvant chemotherapy following surgical resection of bronchogenic carcinoma. All 4 cases were from a subgroup of 19 of these 243 patients who developed pancytopenia while taking busulfan 5 to 8 years before leukemia became clinically apparent. These findings suggest that busulfan is leukemogenic, although its mode of action is uncertain.

Ovarian suppression and amenorrhea with menopausal symptoms commonly occur during busulfan therapy in premenopausal patients. Busulfan has been associated with ovarian failure including failure to achieve puberty in females. Busulfan interferes with spermatogenesis in experimental animals, and there have been clinical reports of sterility, azoospermia, and testicular atrophy in male patients.

Hepatic veno-occlusive disease, which may be life threatening, has been reported in patients receiving busulfan, usually in combination with cyclophosphamide or other chemotherapeutic agents prior to bone marrow transplantation. Possible risk factors for the development of hepatic veno-occlusive disease include: total busulfan dose exceeding 16 mg/kg based on ideal body weight, and concurrent use of multiple alkylating agents (see CLINICAL PHARMACOLOGY and Drug Interactions).

A clear cause-and-effect relationship with busulfan has not been demonstrated. Periodic measurement of serum transaminases, alkaline phosphatase, and bilirubin is indicated for early detection of hepatotoxicity. A reduced incidence of hepatic veno-occlusive disease and other regimen-related toxicities have been observed in patients treated with high-dose MYLERAN and cyclophosphamide when the first dose of cyclophosphamide has been delayed for >24 hours after the last dose of busulfan (see CLINICAL PHARMACOLOGY and Drug Interactions).

Cardiac tamponade has been reported in a small number of patients with thalassemia (2% in one series) who received busulfan and cyclophosphamide as the preparatory regimen for bone marrow transplantation. In this series, the cardiac tamponade was often fatal. Abdominal pain and vomiting preceded the tamponade in most patients.

Pregnancy

Busulfan may cause fetal harm when administered to a pregnant woman. Although there have been a number of cases reported where apparently normal children have been born after busulfan treatment during pregnancy, one case has been cited where a malformed baby was delivered by a mother treated with busulfan. During the pregnancy that resulted in the malformed infant, the mother received x-ray therapy early in the first trimester, mercaptopurine until the third month, then busulfan until delivery. In pregnant rats, busulfan produces sterility in both male and female offspring due to the absence of germinal cells in testes and ovaries. Germinal cell aplasia or sterility in offspring of mothers receiving busulfan during pregnancy has not been reported in humans. There are no adequate and well-controlled studies in pregnant women. If this drug is used during pregnancy, or if the patient becomes pregnant while taking this drug, the patient should be apprised of the potential hazard to the fetus. Women of childbearing potential should be advised to avoid becoming pregnant.

PRECAUTIONS

General

The most consistent, dose-related toxicity is bone marrow suppression. This may be manifest by anemia, leukopenia, thrombocytopenia, or any combination of these. It is imperative that patients be instructed to report promptly the development of fever, sore throat, signs of local infection, bleeding from any site, or symptoms suggestive of anemia. Any one of these findings may indicate busulfan toxicity; however, they may also indicate transformation of the disease to an acute “blastic” form. Since busulfan may have a delayed effect, it is important to withdraw the medication temporarily at the first sign of an abnormally large or exceptionally rapid fall in any of the formed elements of the blood. Patients should never be allowed to take the drug without close medical supervision.

Seizures have been reported in patients receiving busulfan. As with any potentially epileptogenic drug, caution should be exercised when administering busulfan to patients with a history of seizure disorder, head trauma, or receiving other potentially epileptogenic drugs. Some investigators have used prophylactic anticonvulsant therapy in this setting.

Information for Patients

Patients beginning therapy with busulfan should be informed of the importance of having periodic blood counts and to immediately report any unusual fever or bleeding. Aside from the major toxicity of myelosuppression, patients should be instructed to report any difficulty in breathing, persistent cough, or congestion. They should be told that diffuse pulmonary fibrosis is an infrequent, but serious and potentially life-threatening complication of long-term busulfan therapy. Patients should be alerted to report any signs of abrupt weakness, unusual fatigue, anorexia, weight loss, nausea and vomiting, and melanoderma that could be associated with a syndrome resembling adrenal insufficiency. Patients should never be allowed to take the drug without medical supervision and they should be informed that other encountered toxicities to busulfan include infertility, amenorrhea, skin hyperpigmentation, drug hypersensitivity, dryness of the mucous membranes, and rarely, cataract formation. Women of childbearing potential should be advised to avoid becoming pregnant. The increased risk of a second malignancy should be explained to the patient.

Laboratory Tests

It is recommended that evaluation of the hemoglobin or hematocrit, total white blood cell count and differential count, and quantitative platelet count be obtained weekly while the patient is on busulfan therapy. In cases where the cause of fluctuation in the formed elements of the peripheral blood is obscure, bone marrow examination may be useful for evaluation of marrow status. A decision to increase, decrease, continue, or discontinue a given dose of busulfan must be based not only on the absolute hematologic values, but also on the rapidity with which changes are occurring. The dosage of busulfan may need to be reduced if this agent is combined with other drugs whose primary toxicity is myelosuppression. Occasional patients may be unusually sensitive to busulfan administered at standard dosage and suffer neutropenia or thrombocytopenia after a relatively short exposure to the drug. Busulfan should not be used where facilities for complete blood counts, including quantitative platelet counts, are not available at weekly (or more frequent) intervals.

Drug Interactions

Busulfan may cause additive myelosuppression when used with other myelosuppressive drugs.

In one study, 12 of approximately 330 patients receiving continuous busulfan and thioguanine therapy for treatment of chronic myelogenous leukemia were found to have portal hypertension and esophageal varices associated with abnormal liver function tests. Subsequent liver biopsies were performed in 4 of these patients, all of which showed evidence of nodular regenerative hyperplasia. Duration of combination therapy prior to the appearance of esophageal varices ranged from 6 to 45 months. With the present analysis of the data, no cases of hepatotoxicity have appeared in the busulfan-alone arm of the study. Long-term continuous therapy with thioguanine and busulfan should be used with caution.

Busulfan-induced pulmonary toxicity may be additive to the effects produced by other cytotoxic agents.

The concomitant systemic administration of itraconazole to patients receiving high-dose MYLERAN may result in reduced busulfan clearance (see CLINICAL PHARMACOLOGY). Patients should be monitored for signs of busulfan toxicity when itraconazole is used concomitantly with MYLERAN.

Carcinogenesis, Mutagenesis, Impairment of Fertility

See WARNINGS section. The World Health Organization has concluded that there is a causal relationship between busulfan exposure and the development of secondary malignancies.

Pregnancy

Teratogenic Effects: See WARNINGS section.

Nonteratogenic Effects: There have been reports in the literature of small infants being born after the mothers received busulfan during pregnancy, in particular, during the third trimester. One case was reported where an infant had mild anemia and neutropenia at birth after busulfan was administered to the mother from the eighth week of pregnancy to term.

Lactation

It is not known whether this drug is excreted in human milk. Because of the potential for tumorigenicity shown for busulfan in animal and human studies, a decision should be made whether to discontinue nursing or to discontinue the drug, taking into account the importance of the drug to the mother.

Pediatric Use

See INDICATIONS AND USAGE and DOSAGE AND ADMINISTRATION sections.

Geriatric Use

Clinical studies of busulfan did not include sufficient numbers of subjects aged 65 and over to determine whether they respond differently from younger subjects. Other reported clinical experience has not identified differences in responses between the elderly and younger patients. In general, dose selection for an elderly patient should be cautious, usually starting at the low end of the dosing range, reflecting the greater frequency of decreased hepatic, renal, or cardiac function, and of concomitant disease or other drug therapy.

ADVERSE REACTIONS

To report SUSPECTED ADVERSE REACTIONS, contact Waylis Therapeutics LLC Toll-Free at 1-888-514-4727 or FDA at 1-800-FDA-1088 or www.fda.gov/medwatch.

Hematological Effects

The most frequent, serious, toxic effect of busulfan is dose-related myelosuppression resulting in leukopenia, thrombocytopenia, and anemia. Myelosuppression is most frequently the result of a failure to discontinue dosage in the face of an undetected decrease in leukocyte or platelet counts.

Aplastic anemia (sometimes irreversible) has been reported rarely, often following long-term conventional doses and also high doses of MYLERAN.

Pulmonary

Interstitial pulmonary fibrosis has been reported rarely, but it is a clinically significant adverse effect when observed and calls for immediate discontinuation of further administration of the drug. The role of corticosteroids in arresting or reversing the fibrosis has been reported to be beneficial in some cases and without effect in others.

Cardiac

Cardiac tamponade has been reported in a small number of patients with thalassemia who received busulfan and cyclophosphamide as the preparatory regimen for bone marrow transplantation (see WARNINGS).

One case of endocardial fibrosis has been reported in a 79-year-old woman who received a total dose of 7,200 mg of busulfan over a period of 9 years for the management of chronic myelogenous leukemia. At autopsy, she was found to have endocardial fibrosis of the left ventricle in addition to interstitial pulmonary fibrosis.

Ocular

Busulfan is capable of inducing cataracts in rats and there have been several reports indicating that this is a rare complication in humans.

Dermatologic

Hyperpigmentation is the most common adverse skin reaction and occurs in 5% to 10% of patients, particularly those with a dark complexion.

Metabolic

In a few cases, a clinical syndrome closely resembling adrenal insufficiency and characterized by weakness, severe fatigue, anorexia, weight loss, nausea and vomiting, and melanoderma has developed after prolonged busulfan therapy. The symptoms have sometimes been reversible when busulfan was withdrawn. Adrenal responsiveness to exogenously administered ACTH has usually been normal. However, pituitary function testing with metyrapone revealed a blunted urinary 17-hydroxycorticosteroid excretion in 2 patients. Following the discontinuation of busulfan (which was associated with clinical improvement), rechallenge with metyrapone revealed normal pituitary-adrenal function.

Hyperuricemia and/or hyperuricosuria are not uncommon in patients with chronic myelogenous leukemia. Additional rapid destruction of granulocytes may accompany the initiation of chemotherapy and increase the urate pool. Adverse effects can be minimized by increased hydration, urine alkalinization, and the prophylactic administration of a xanthine oxidase inhibitor such as allopurinol.

Hepatic Effects

Esophageal varices have been reported in patients receiving continuous busulfan and thioguanine therapy for treatment of chronic myelogenous leukemia (see PRECAUTIONS: Drug Interactions). Hepatic veno-occlusive disease has been observed in patients receiving busulfan (see WARNINGS).

Miscellaneous

Other reported adverse reactions include: urticaria, erythema multiforme, erythema nodosum, alopecia, porphyria cutanea tarda, excessive dryness and fragility of the skin with anhidrosis, dryness of the oral mucous membranes and cheilosis, gynecomastia, cholestatic jaundice, and myasthenia gravis. Most of these are single case reports, and in many, a clear cause-and-effect relationship with busulfan has not been demonstrated.

Seizures (see PRECAUTIONS: General) have been observed in patients receiving higher than recommended doses of busulfan.

Observed During Clinical Practice

The following events have been identified during post-approval use of busulfan. Because they are reported voluntarily from a population of unknown size, estimates of frequency cannot be made. These events have been chosen for inclusion due to a combination of their seriousness, frequency of reporting, or potential causal connection to busulfan.

Blood and Lymphatic: Aplastic anemia.

Eye: Cataracts, corneal thinning, lens changes.

Hepatobiliary Tract and Pancreas: Centrilobular sinusoidal fibrosis, hepatic veno-occlusive disease, hepatocellular atrophy, hepatocellular necrosis, hyperbilirubinemia (see WARNINGS).

Non-site Specific: Infection, mucositis, sepsis.

Respiratory: Pneumonia.

Skin: Rash. An increased local cutaneous reaction has been observed in patients receiving radiotherapy soon after busulfan.

OVERDOSAGE

There is no known antidote to busulfan. The principal toxic effects are bone marrow depression and pancytopenia. The hematologic status should be closely monitored and vigorous supportive measures instituted if necessary. Induction of vomiting or gastric lavage followed by administration of charcoal would be indicated if ingestion were recent. Dialysis may be considered in the management of overdose as there is 1 report of successful dialysis of busulfan (see CLINICAL PHARMACOLOGY).

Gastrointestinal toxicity with mucositis, nausea, vomiting, and diarrhea has been observed when MYLERAN was used in association with bone marrow transplantation.

Oral LD50 single doses in mice are 120 mg/kg. Two distinct types of toxic response are seen at median lethal doses given intraperitoneally. Within a matter of hours there are signs of stimulation of the central nervous system with convulsions and death on the first day. Mice are more sensitive to this effect than are rats. With doses at the LD50 there is also delayed death due to damage to the bone marrow. At 3 times the LD50, atrophy of the mucosa of the large intestine is found after a week, whereas that of the small intestine is little affected. After doses in the order of 10 times those used therapeutically were added to the diet of rats, irreversible cataracts were produced after several weeks. Small doses had no such effect.

DOSAGE AND ADMINISTRATION

Busulfan is administered orally. The usual adult dose range for remission induction is 4 to 8 mg, total dose, daily. Dosing on a weight basis is the same for both pediatric patients and adults, approximately 60 mcg/kg of body weight or 1.8 mg/m^2 of body surface, daily. Since the rate of fall of the leukocyte count is dose related, daily doses exceeding 4 mg per day should be reserved for patients with the most compelling symptoms; the greater the total daily dose, the greater is the possibility of inducing bone marrow aplasia.

A decrease in the leukocyte count is not usually seen during the first 10 to 15 days of treatment; the leukocyte count may actually increase during this period and it should not be interpreted as resistance to the drug, nor should the dose be increased. Since the leukocyte count may continue to fall for more than 1 month after discontinuing the drug, it is important that busulfan be discontinued prior to the total leukocyte count falling into the normal range. When the total leukocyte count has declined to approximately 15,000/mcL, the drug should be withheld.

With a constant dose of busulfan, the total leukocyte count declines exponentially; a weekly plot of the leukocyte count on semi-logarithmic graph paper aids in predicting the time when therapy should be discontinued. With the recommended dose of busulfan, a normal leukocyte count is usually achieved in 12 to 20 weeks.

During remission, the patient is examined at monthly intervals and treatment resumed with the induction dosage when the total leukocyte count reaches approximately 50,000/mcL. When remission is shorter than 3 months, maintenance therapy of 1 to 3 mg daily may be advisable in order to keep the hematological status under control and prevent rapid relapse.

Procedures for proper handling and disposal of anticancer drugs should be considered. Several guidelines on this subject have been published.^1-8

There is no general agreement that all of the procedures recommended in the guidelines are necessary or appropriate.

HOW SUPPLIED

MYLERAN is supplied as white, film-coated, round, biconvex tablets containing 2 mg busulfan in amber glass bottles with child-resistant closures. One side is imprinted with "GX EF3" and the other side is imprinted with an "M.”

Bottle of 25 (NDC 80725-620-25).

Store at 25°C (77°F); excursions permitted to 15° to 30°C (59° to 86°F) (see USP Controlled Room Temperature).

REFERENCES

1. ONS Clinical Practice Committee. Cancer Chemotherapy Guidelines and Recommendations for Practice. Pittsburgh, PA. Oncology Nursing Society; 1999:32-41.
2. Recommendations for the safe handling of parenteral antineoplastic drugs. Washington, DC: Division of Safety, Clinical Center Pharmacy Department and Cancer Nursing Services, National Institutes of Health and Human Services; 1992. US Dept of Health and Human Services, Public Health Service publication NIH 92-2621.
3. AMA Council on Scientific Affairs. Guidelines for handling parenteral antineoplastics. JAMA. 1985;253:1590-1591.
4. National Study Commission on Cytotoxic Exposure. Recommendations for handling cytotoxic agents. 1987. Available from Louis P. Jeffrey, Chairman, National Study Commission on Cytotoxic Exposure. Massachusetts College of Pharmacy and Allied Health Sciences, 179 Longwood Avenue, Boston, MA 02115.
5. Clinical Oncological Society of Australia. Guidelines and recommendations for safe handling of antineoplastic agents. Med J Australia. 1983;1:426-428.
6. Jones RB, Frank R, Mass T. Safe handling of chemotherapeutic agents: a report from the Mount Sinai Medical Center. CA-A Cancer J for Clin. 1983;33:258-263.
7. American Society of Hospital Pharmacists. ASHP technical assistance bulletin on handling cytotoxic and hazardous drugs. Am J Hosp Pharm. 1990;47:1033-1049.
8. Controlling Occupational Exposure to Hazardous Drugs. (OSHA Work-Practice Guidelines.) Am J. Health-Syst Pharm. 1996:53:1669-1685.

Distributed by: Waylis Therapeutics LLC
Wixom, MI 48393
Made in Germany
Rev. 02/2023

PACKAGE LABEL

Principal Display Panel

NDC 80725-620-25

MYLERAN®
(busulfan) Tablets

2 mg

25 Tablets

Each tablet contains 2 mg busulfan.

Rx only